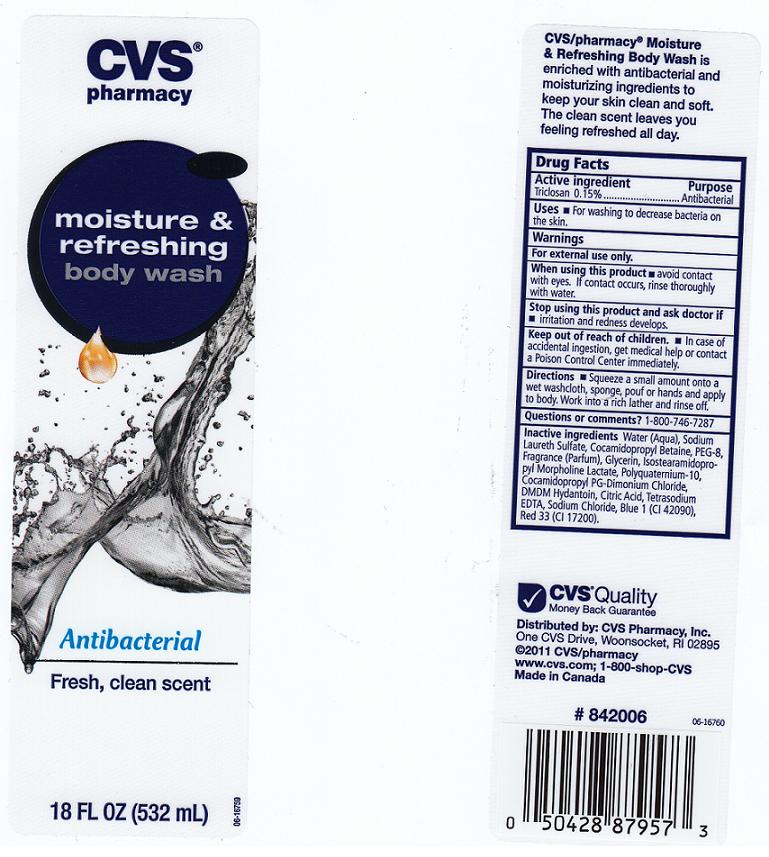 DRUG LABEL: Antibacterial Body Wash
NDC: 59779-805 | Form: LIQUID
Manufacturer: CVS Pharmacy
Category: otc | Type: HUMAN OTC DRUG LABEL
Date: 20110627

ACTIVE INGREDIENTS: TRICLOSAN 0.15 mL/100 mL
INACTIVE INGREDIENTS: WATER; SODIUM LAURETH SULFATE; COCAMIDOPROPYL BETAINE; POLYETHYLENE GLYCOL 900; GLYCERIN; DMDM HYDANTOIN; CITRIC ACID MONOHYDRATE; EDETATE SODIUM; SODIUM CHLORIDE; FD&C BLUE NO. 1; D&C RED NO. 33; ISOSTEARAMIDOPROPYL MORPHOLINE LACTATE; POLYQUATERNIUM-10 (400 CPS AT 2%); COCAMIDOPROPYL PG-DIMONIUM CHLORIDE PHOSPHATE

Drug Facts

Active Ingredient

Triclosan 0.15%

Purpose

Antibacterial

USES

For washing to decrease bacteria on the skin.

WARNINGS

FOR EXTERNAL USE ONLY.

WHEN USING THIS PRODUCT

AVOID CONTACT WITH EYES. IF CONTACT OCCURS, RINSE THROUGHLY WITH WATER.

STOP USING THIS PRODUCT AND ASK DOCTOR IF

IRRITATION AND REDNESS DEVELOPS.

KEEP OUT OF REACH OF CHILDREN

IN CASE OF ACCIDENTAL INGESTION, GET MEDICAL HELP OR CONTACT A POISON CONTROL CENTER IMMEDIATELY.

DIRECTIONS

SQUEEZE A SMALL AMOUNT ONTO A WET WASHCLOTH, SPONGE, POUF OR HANDS AND APPLY TO BODY. WORK INTO A RICH LATHER AND RINSE OFF.

QUESTIONS OR COMMENTS?

1-800-746-7287

INACTIVE INGREDIENTS

WATER, SODIUM LAURETH SULFATE, COCAMIDOPROPYL BETAINE, PEG-8, FRAGRANCE, GLYCERIN, ISOSTEARAMIDOPROPYLMORPHOLINE LACTATE, POLYQUATERNIUM-10, COCAMIDOPROPYL PG-DIMONIUM CHLORIDE, DMDM HYDANTOIN, CITRIC ACID, TETRASODIUM EDTA, SODIUM CHLORIDE, BLUE 1 (CI42090), RED 33 (CI 17200).